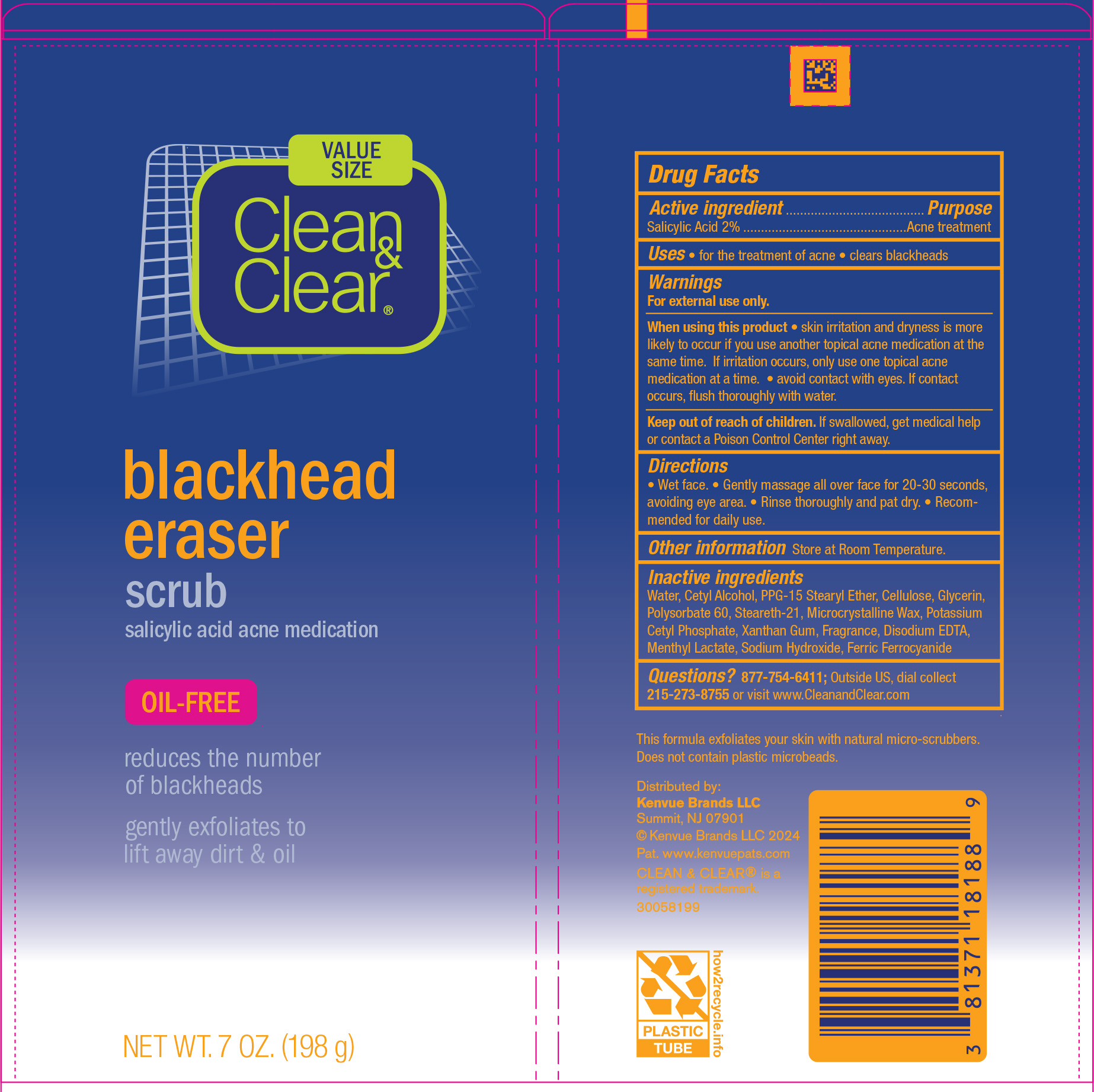 DRUG LABEL: Clean and Clear blackhead eraser scrub
NDC: 69968-0234 | Form: CREAM
Manufacturer: Kenvue Brands LLC
Category: otc | Type: HUMAN OTC DRUG LABEL
Date: 20241211

ACTIVE INGREDIENTS: SALICYLIC ACID 20 mg/1 g
INACTIVE INGREDIENTS: WATER; CETYL ALCOHOL; PPG-15 STEARYL ETHER; STEARETH-21; POLYSORBATE 60; POWDERED CELLULOSE; GLYCERIN; MICROCRYSTALLINE WAX; POTASSIUM CETYL PHOSPHATE; XANTHAN GUM; SODIUM HYDROXIDE; EDETATE DISODIUM; METHYL LACTATE, (-)-; FERRIC FERROCYANIDE

Clean & Clear® blackhead eraser® scrub

Drug Facts

Active ingredients

Salicylic Acid 2%

Purpose

Acne treatment

Uses

- for the treatment of acne
- clears blackheads

Warnings

For external use only.

When using this product

- skin irritation and dryness is more likely to occur if you use another topical acne medication at the same time. If irritation occurs, only use one topical acne medication at a time.
- avoid contact with eyes. If contact occurs, flush thoroughly with water.

Keep out of reach of children. If swallowed, get medical help or contact a Poison Control Center right away.

Directions

- Wet face.
- Gently massage all over face for 20-30 seconds, avoiding eye area.
- Rinse thoroughly and pat dry.
- Recommended for daily use.

Other information

Store at Room Temperature.

Inactive ingredients

Water, Cetyl alcohol, PPG-15 Stearyl Ether, Cellulose, Glycerin, Polysorbate 60, Steareth-21, Microcrystalline Wax, Potassium Cetyl Phosphate, Xanthan Gum, Fragrance, Disodium EDTA, Methyl Lactate, Sodium Hydroxide, Ferric Ferrocyanide

Questions?

877-754-6411; Outside US, dial collect 215-273-8755 or visit www.CleanandClear.com

Distributed by:
Kenvue Brands LLC
Summit, NJ 07901

PRINCIPAL DISPLAY PANEL - 198 g Tube Label

VALUE
SIZE

Clean
&
Clear®

blackhead
eraser
scrub
salicylic acid acne medication

OIL-FREE

reduces the number
of blackheads

gently exfoliates to
lift away dirt & oil

NET WT. 7 OZ. (198 g)